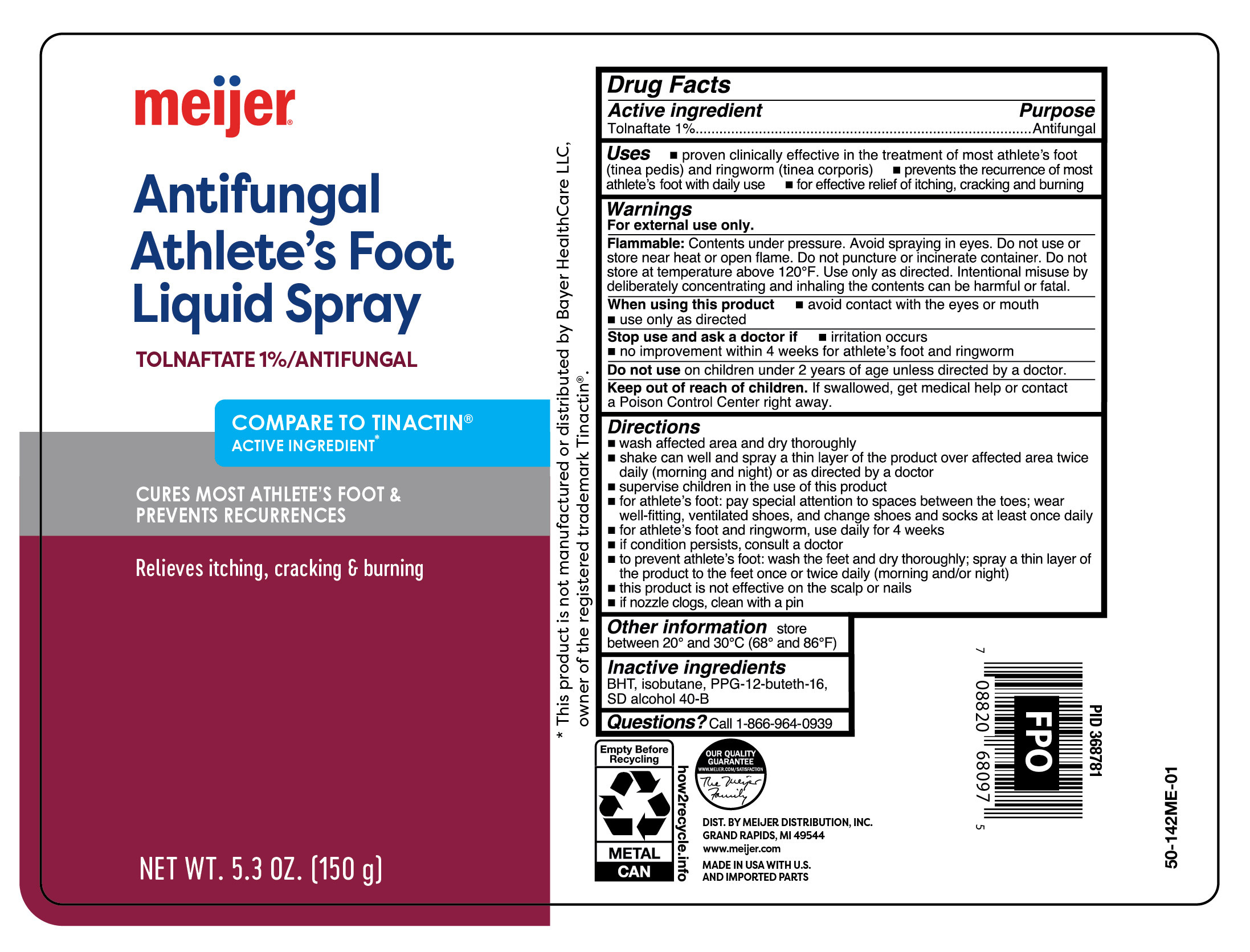 DRUG LABEL: Tolnaftate
NDC: 79481-0625 | Form: AEROSOL, SPRAY
Manufacturer: Meijer Distribution Inc.
Category: otc | Type: HUMAN OTC DRUG LABEL
Date: 20260120

ACTIVE INGREDIENTS: TOLNAFTATE 10 mg/1 g
INACTIVE INGREDIENTS: BUTYLATED HYDROXYTOLUENE; ISOBUTANE; PPG-12-BUTETH-16; ALCOHOL

Meijer Antifungal Tolnaftate Liquid Spray

Active ingredient

Tolnaftate 1%

Purpose

Antifungal

Uses

- proven clinically effective in the treatment of most athlete's foot (tinea pedis) and ringworm (tinea corporis)
- prevent recurrence of most athlete's foot with daily use
- for effective relief of itching, cracking and burning

Warnings

For external use only.

Flammable:

Contents under pressue. Avoid spraying in eyes. Do not use or store near heat or open flame. Do not puncture or incinerate container. Do not store at temperature above 120F. Keep out of reach of children. Use only as directed. Intentional misuse by dilberately concentrating and inhaling the contents can be harmful or fatal.

When using this product

avoid contact with the eyes or mouth

use only as directed

Stop use and ask a doctor if

irritation occurs

no improvement within 4 weeks for athlete's foot and ringworm

Do not use

on children under 2 years of age unless directed by a doctor.

Keep out of reach od children.

If swallowed, get medical hel or contact a Poison Control Center right away.

Directions

- wash affected area and dry thoroughly
- shake can well and spray a thin layer of the product over affected area twice daily (morning and night) or as directed by a doctor
- supervise children in the use of this product
- for athlete's foot: pay special attention to spaces between the toes; wear well-fitting, ventilated shoes, and change shoes and socks at least once daily
- for athlete's foot and ringworm, use daily for 4 weeks
- if condition persists, consult a doctor
- to prevent athlete's foot: wash the feet and dry thoroughly; spray a thin layer of the product to the feet once or twice daily (morning and/or night)
- this product is not effective on the scalp or nails
- if nozzle clogs, clean with a pin

Other information

store between 20º and 30ºC (68º and 86ºF)

Inactive ingredients

BHT, isobutane, PPG-12-buteth-16, SD alcohol 40-B

Questions?

Call 1-866-964-0939

Principal Display Panel

Meijer

Antifungal

Athlete's Foot

Liquid Spray

Tolnaftate 1%/ANTIFUNGAL

- Cures Most Athlete's Foot & Prevents Recurrences
- Relieves Itching, Cracking & Burning

NET WT 5.3 OZ (150g)